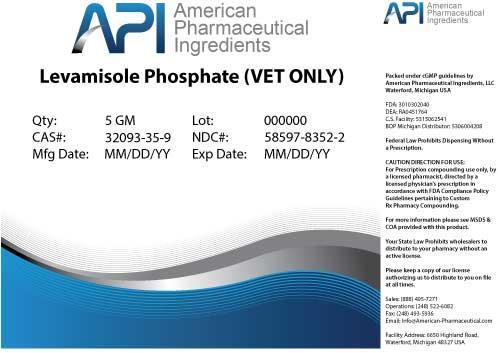 DRUG LABEL: Levamisole Phosphate
NDC: 58597-8352 | Form: POWDER
Manufacturer: AMERICAN PHARMACEUTICAL INGREDIENTS LLC
Category: other | Type: BULK INGREDIENT
Date: 20140428

ACTIVE INGREDIENTS: Levamisole Phosphate 1 g/1 g

Levamisole Phosphate